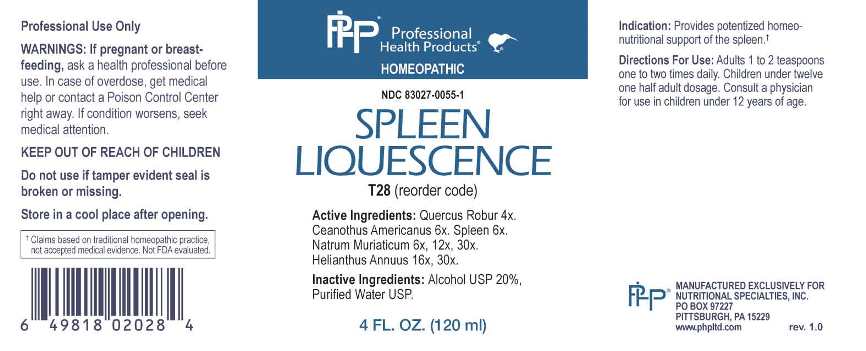 DRUG LABEL: Spleen Liquescence
NDC: 83027-0055 | Form: LIQUID
Manufacturer: Nutritional Specialties, Inc.
Category: homeopathic | Type: HUMAN OTC DRUG LABEL
Date: 20230330

ACTIVE INGREDIENTS: QUERCUS ROBUR TWIG BARK 4 [hp_Q]/1 mL; CEANOTHUS AMERICANUS LEAF 6 [hp_X]/1 mL; BOS TAURUS SPLEEN 6 [hp_X]/1 mL; SODIUM CHLORIDE 6 [hp_X]/1 mL; HELIANTHUS ANNUUS FLOWERING TOP 16 [hp_X]/1 mL
INACTIVE INGREDIENTS: WATER; ALCOHOL

DRUG FACTS:

ACTIVE INGREDIENTS:

Quercus Robur 4X, Ceanothus Americanus 6X, Spleen 6X, Natrum Muriaticum 6X, 12X, 30X, Helianthus Annuus 16X, 30X.

PURPOSE:

Provides potentized homeo-nutritional support of the spleen.†

†Claims based on traditional homeopathic practice, not accepted medical evidence. Not FDA evaluated.

WARNINGS:

Professional Use Only

If pregnant or breast-feeding, ask a health professional before use.

In case of overdose, get medical help or contact a Poison Control Center right away.

If condition worsens, seek medical attention.

KEEP OUT OF REACH OF CHILDREN

Do not use if tamper evident seal is broken or missing.

Store in a cool place after opening

KEEP OUT OF REACH OF CHILDREN:

In case of overdose, get medical help or contact a Poison Control Center right away.

DIRECTIONS:

Adults 1 to 2 teaspoons one to two times daily. Children under twelve one half adult dosage. Consult a physician for use in children under 12 years of age.

INDICATIONS:

Provides potentized homeo-nutritional support of the spleen.†

†Claims based on traditional homeopathic practice, not accepted medical evidence. Not FDA evaluated.

INACTIVE INGREDIENTS:

Alcohol USP 20%, Purified Water USP.

QUESTIONS:

MANUFACTURED EXCLUSIVELY FOR

NUTRITIONAL SPECIALTIES, INC.

PO BOX 97227

PITTSBURG, PA 15229

www.phpltd.com

PACKAGE LABEL DISPLAY:

Professional

Health Products

HOMEOPATHIC

NDC 83027-0055-1

SPLEEN

LIQUESCENCE

4 FL. OZ (120 ml)